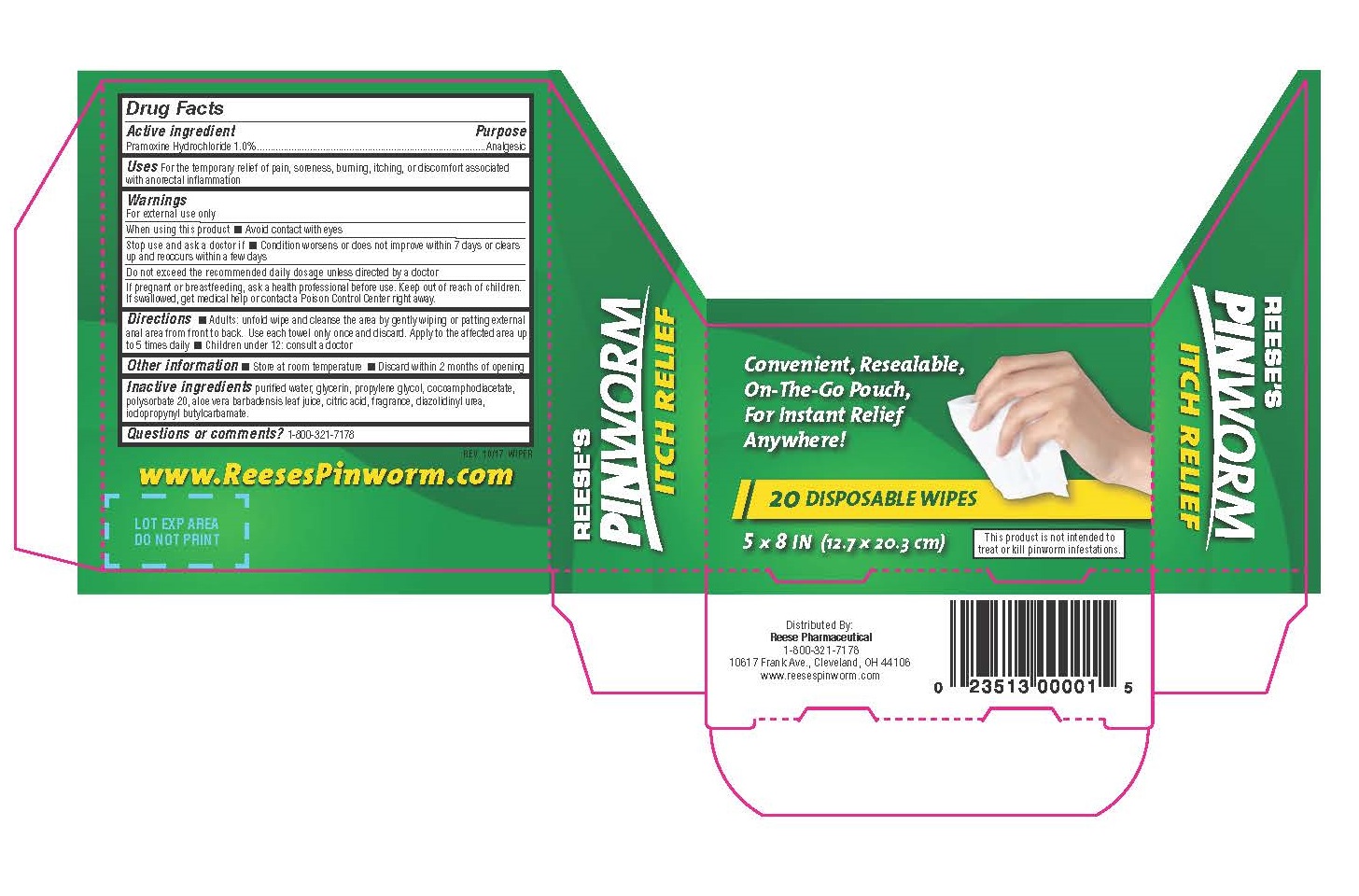 DRUG LABEL: Reeses
NDC: 10956-799 | Form: CLOTH
Manufacturer: Reese Pharmaceutical Co
Category: otc | Type: HUMAN OTC DRUG LABEL
Date: 20171002

ACTIVE INGREDIENTS: PRAMOXINE HYDROCHLORIDE 10 mg/1 g
INACTIVE INGREDIENTS: WATER; GLYCERIN; PROPYLENE GLYCOL; DISODIUM COCOAMPHODIACETATE; POLYSORBATE 20; ALOE VERA LEAF; CITRIC ACID MONOHYDRATE; DIAZOLIDINYL UREA; IODOPROPYNYL BUTYLCARBAMATE

Reeses PINWORM Itch Relief - Drug Facts Label

Active ingredient

Pramoxine Hydrochloride 1.0% w/w

Purpose

ANALGESIC

Uses

- Temporarily relieves itching

Warnings

For external use only

When using this product

- Avoid contact with eyes

Stop use and ask a doctor if

- Condition worsens or does not improve within 7 days or clears up and reoccurs within a few days

Keep out of the reach of children.

If swallowed, get medical help or contact a Poison Control Center right away.

Direction

- Adults: unfold wipe and cleanse the area by gently wiping or patting external area from front to back. Use each wipe only once and discard.
- Use up to 5 times daily.
- Children under 12: consult a doctor

Other information

- Store at room temperature
- Discard within 2 months of opening

Inactive ingredients

purified water, glycerin, propylene glycol, cocoamphodiacetate, polysorbate 20, aloe vera barbadensis leaf juice, citric acid, fragrance, diazolidinyl urea, iodopropynyl butylcarbamate.

Questions or comments?

1-800-321-7178